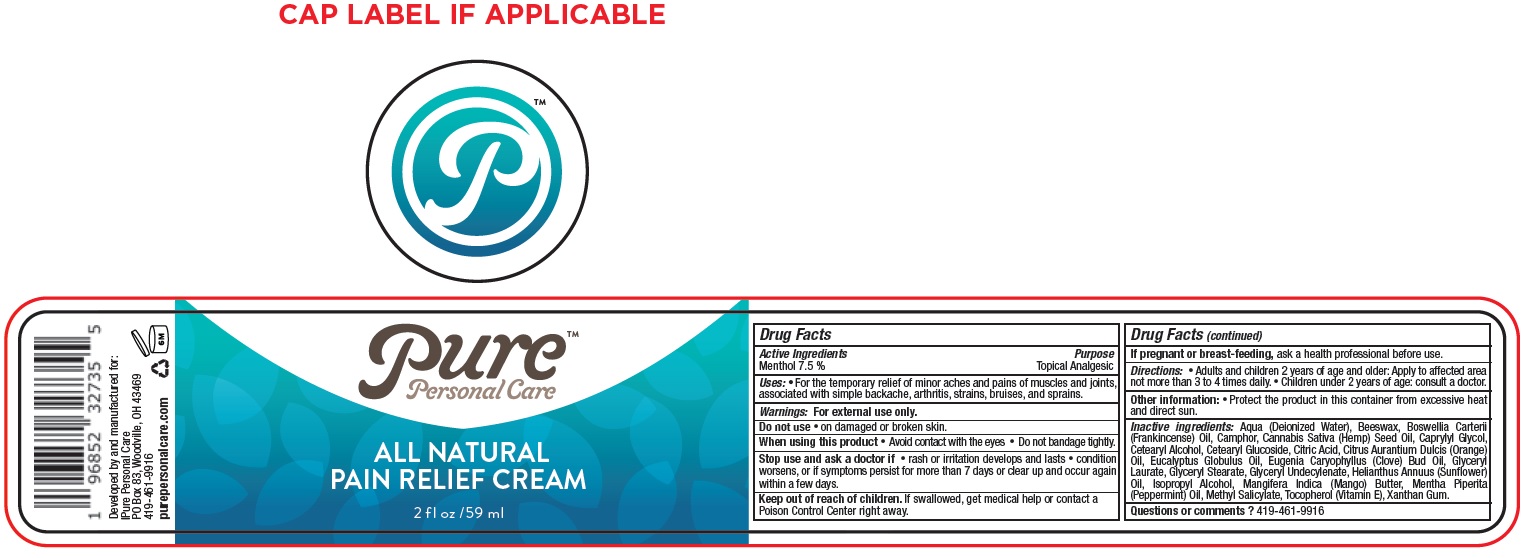 DRUG LABEL: PURE PERSONAL All Natural Pain Relief Cream
NDC: 83072-374 | Form: CREAM
Manufacturer: PURE PERSONAL CARE, LLC
Category: otc | Type: HUMAN OTC DRUG LABEL
Date: 20231106

ACTIVE INGREDIENTS: MENTHOL 75 mg/1 mL
INACTIVE INGREDIENTS: WATER; YELLOW WAX; FRANKINCENSE OIL; CANNABIS SATIVA SEED OIL; CAPRYLYL GLYCOL; CETOSTEARYL ALCOHOL; CETEARYL GLUCOSIDE; CITRIC ACID MONOHYDRATE; ORANGE OIL, COLD PRESSED; EUCALYPTUS OIL; CLOVE OIL; GLYCERYL LAURATE; GLYCERYL MONOSTEARATE; HELIANTHUS ANNUUS FLOWERING TOP; ISOPROPYL ALCOHOL; MANGO; PEPPERMINT OIL; METHYL SALICYLATE; TOCOPHEROL; XANTHAN GUM

PURE PERSONAL All Natural Pain Relief Cream

Active Ingredients

Menthol 7.5 %

Purpose

Topical Analgesic

Uses:

• For the temporary relief of minor aches and pains of muscles and joints, associated with simple backache, arthritis, strains, bruises, and sprains.

Warnings:

For external use only.

Do not use

• on damaged or broken skin.

When using this product

• Avoid contact with the eyes • Do not bandage tightly.

Stop use and ask a doctor if

• rash or irritation develops and lasts • condition worsens, or if symptoms persist for more than 7 days or clear up and occur again within a few days.

Keep out of reach of children.

If swallowed, get medical help or contact a Poison Control Center right away.

If pregnant or breast-feeding,

ask a health professional before use.

Directions:

• Adults and children 2 years of age and older: Apply to affected area not more than 3 to 4 times daily. • Children under 2 years of age: consult a doctor.

Other information:

• Protect the product in this container from excessive heat and direct sun.

Inactive ingredients:

Aqua (Deionized Water), Beeswax, Boswellia Carterii (Frankincense) Oil, Camphor, Cannabis Sativa (Hemp) Seed Oil, Caprylyl Glycol, Cetearyl Alcohol, Cetearyl Glucoside, Citric Acid, Citrus Aurantium Dulcis (Orange) Oil, Eucalyptus Globulus Oil, Eugenia Caryophyllus (Clove) Bud Oil, Glyceryl Laurate, Glyceryl Stearate, Glyceryl Undecylenate, Helianthus Annuus (Sunflower) Oil, Isopropyl Alcohol, Mangifera Indica (Mango) Butter, Mentha Piperita (Peppermint) Oil, Methyl Salicylate, Tocopherol (Vitamin E), Xanthan Gum.

Questions or comments?

419-461-9916